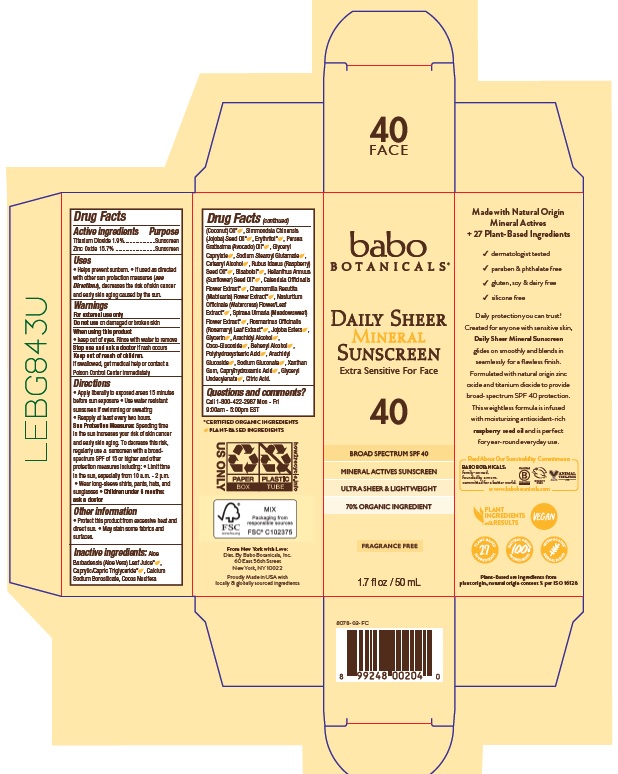 DRUG LABEL: Babo Botanicals Daily Sheer Mineral Sunscreen SPF 40
NDC: 79265-8078 | Form: LOTION
Manufacturer: Babo Botanicals, Inc.
Category: otc | Type: HUMAN OTC DRUG LABEL
Date: 20241212

ACTIVE INGREDIENTS: ZINC OXIDE 157 mg/1 mL; TITANIUM DIOXIDE 19 mg/1 mL
INACTIVE INGREDIENTS: ARACHIDYL ALCOHOL; POLYHYDROXYSTEARIC ACID (2300 MW); ARACHIDYL GLUCOSIDE; CAPRYLHYDROXAMIC ACID; GLYCERYL 1-UNDECYLENATE; CETOSTEARYL ALCOHOL; FILIPENDULA ULMARIA FLOWER; ROSEMARY; JOJOBA OIL; XANTHAN GUM; SUNFLOWER OIL; ALOE VERA LEAF; MEDIUM-CHAIN TRIGLYCERIDES; COCONUT OIL; AVOCADO OIL; ERYTHRITOL; GLYCERYL CAPRYLATE; RASPBERRY SEED OIL; SODIUM STEAROYL GLUTAMATE; COCO GLUCOSIDE; LEVOMENOL; CALENDULA OFFICINALIS FLOWER; GLYCERIN; CHAMOMILE; NASTURTIUM OFFICINALE; SODIUM GLUCONATE; JOJOBA OIL, RANDOMIZED; CITRIC ACID MONOHYDRATE

Babo Botanicals Daily Sheer Mineral Sunscreen SPF 40

Active ingredients

Titanium Dioxide 1.9%

Zinc Oxide 15.7%

Purpose

Sunscreen

Uses

- Helps prevent sunburn.
- If used as directed with other sun protection measures (see Directions), decreases the risk of skin cancer and early skin aging caused by the sun.

Warnings

For external use only.

Do not use

on damaged or broken skin.

When using this product

- keep out of eyes. Rinse with water to remove.

Stop use and ask doctor

- if rash occurs.

Keep out of reach of children.

If swallowed, get medical help or contact a Poison Control Center immediately.

Directions

- Apply liberally to exposed areas15 minutes before sun exposure.
- Use water resistant sunscreen if swimming or sweating
- Reapply at least every two hours.

Sun Protection Measures Spending time in the sun increases your risk of skin cancer and early skin aging. To decrease this risk, regularly use a sunscreen with a Broad Spectrum SPF of 15 or higher and other sun protection measures including:

- Limit time in the sun, especially from 10 a.m. - 2 p.m.
- Wear long-sleeve shirts, pants, hats and sunglasses.
- Children under 6 months of age: ask a doctor

Other information

- Protect this product from excessive heat and direct sun.
- May stain some fabrics and surfaces.

Inactive ingredients

Aloe Barbadensis (Aloe Vera) Leaf Juice, Caprylic/Capric Triglyceride, Calcium Sodium Borosilicate, Cocos Nucifera (Coconut) Oil, Simmondsia Chinensis (Jojoba) Seed Oil, Erythritol, Persea Gratissima (Avocado) Oil, Glyceryl Caprylate, Sodium Stearoyl Glutamate, Cetearyl Alcohol, Rubus Idaeus (Raspberry) Seed Oil, Bisabolol, Helianthus Annuus (Sunflower) Seed Oil, Calendula Officinalis Flower Extract, Chamomilla Recutita (Matricaria) Flower Extract, Nasturtium Officinale (Watercress) Flower/Leaf Extract, Spiraea Ulmaria (Meadowsweet) Flower Extract, Rosmarinus Officinalis (Rosemary) Leaf Extract, Jojoba Esters, Glycerin, Arachidyl Alcohol, Coco-Glucoside, Behenyl Alcohol, Polyhydroxystearic Acid, Arachidyl Glucoside, Sodium Gluconate, Xanthan Gum, Caprylhydroxamic Acid, Glyceryl Undecylenate, Citric Acid.

Questions and comments?

Call 1-800-422-2987 Mon - Fri

9:00am - 5:00pm EST